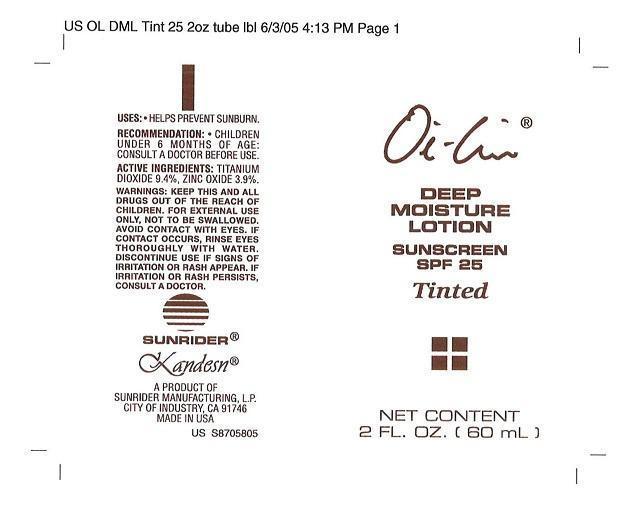 DRUG LABEL: OI LIN DEEP MOISTURE SUNSCREEN SPF 25
NDC: 62191-010 | Form: LOTION
Manufacturer: Sunrider Manufacturing L.P.
Category: otc | Type: HUMAN OTC DRUG LABEL
Date: 20130213

ACTIVE INGREDIENTS: TITANIUM DIOXIDE 94 mg/1 g; ZINC OXIDE     39 mg/1 g
INACTIVE INGREDIENTS: ALOE VERA LEAF; ALUMINUM OXIDE   ; ARCTIUM LAPPA ROOT   ; BUTYLENE GLYCOL; BUTYLPARABEN; CERAMIDE 3; COMFREY ROOT   ; CYCLOMETHICONE 5; CYMBOPOGON SCHOENANTHUS LEAF   ; CYMBOPOGON SCHOENANTHUS OIL   ; ETHYLPARABEN; GLYCERIN; GLYCYRRHIZINATE DIPOTASSIUM; HORSE CHESTNUT; HYDROLYZED WHEAT PROTEIN (ENZYMATIC, 3000 MW); LAMINARIA DIGITATA   ; LAVANDULA ANGUSTIFOLIA FLOWERING TOP; LAVENDER OIL; LEVOMENOL; MATRICARIA RECUTITA; MAGNESIUM SULFATE; MENTHA PULEGIUM   ; METHYLPARABEN; PENNYROYAL OIL; PEG/PPG-18/18 DIMETHICONE; PEG/PPG-20/15 DIMETHICONE; PEG-10 DIMETHICONE (600 CST); PHENOXYETHANOL; PROPYLPARABEN; ROSEMARY; SILICON DIOXIDE   ; SODIUM PYRROLIDONE CARBOXYLATE; SUNFLOWER OIL; TETRAHEXYLDECYL ASCORBATE; ALPHA-TOCOPHEROL ACETATE   ; TOCOPHEROL; TRIETHOXYCAPRYLYLSILANE; EDETATE TRISODIUM   ; WATER

OI LIN DEEP MOISTURE SUNSCREEN SPF 25 TINTED

PURPOSE

USES: HELPS PREVENT SUNBURNS

DOSAGE AND ADMINISTRATION

RECOMMENDATION: APPLY GENEROUSLY TO FACE BEFORE EXPOSURE TO SUN, AVOIDING CONTACT WITH EYES. REAPPLY TO EXPOSED AREAS AS NEEDED THROUGHOUT THE DAY

ASK DOCTOR

CHILDREN UNDER 6 MONTHS OF AGE: CONSULT A DOCTOR BEFORE USE

WARNINGS

WARNING: FOR EXTERNAL USE ONLY, IF SWALLOWED, SEEK MEDICAL HELP OR CONTACT A POISON CONTROL CENTER IMMEDIATELY. IF CONTACT WITH EYES OCCURS, RINSE THOROUGHLY WITH WATER. DISCONTINUE USE AND CONSULT A DOCTOR IF PERSISTENT SIGNS OF IRRITATION OR RASH APPEAR

KEEP OUT OF REACH OF CHILDREN.

ACTIVE INGREDIENTS:
TITANIUM DIOXIDE 9.4%
ZINC OXIDE 3.9%

PACKAGE LABEL

PUMP